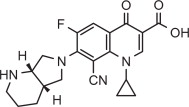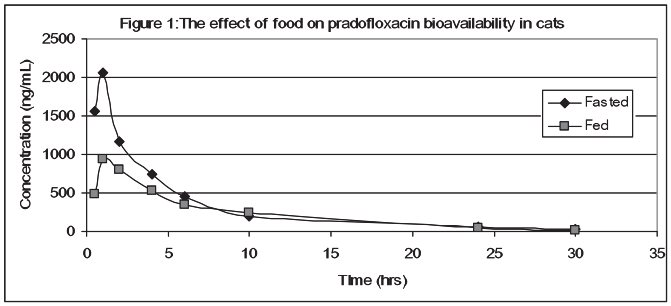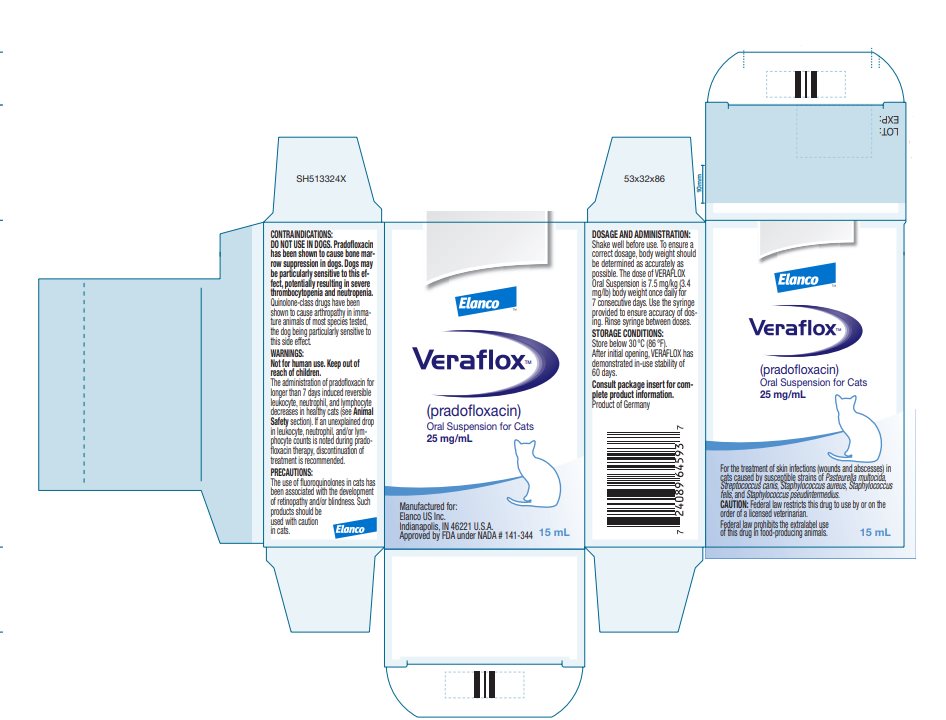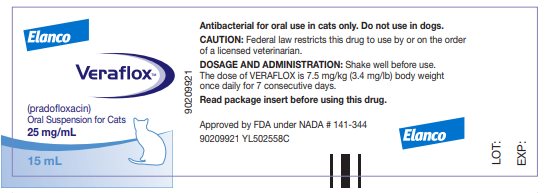 DRUG LABEL: Veraflox
NDC: 58198-0039 | Form: SUSPENSION
Manufacturer: Elanco US Inc.
Category: animal | Type: PRESCRIPTION ANIMAL DRUG LABEL
Date: 20251111

ACTIVE INGREDIENTS: PRADOFLOXACIN 25 mg/1 mL

Veraflox™

Elanco™

(pradofloxacin)

Oral Suspension for Cats

25 mg/mL

Do not use in dogs.

Federal law prohibits the extralabel use of this drug
in food-producing animals.

CAUTION

Federal law restricts this drug to use by or on the order of a licensed veterinarian.

DESCRIPTION

Pradofloxacin is a fluoroquinolone antibiotic and belongs to the class of quinoline carboxylic acid derivatives. Its chemical name is: 7-[(4aS) octahydro-6H-pyrrolo [3, 4-b] pyridine-6yl]-8-cyano-1-cyclopropyl-6-fluoro-4-oxo-1,4-dihydro-3-quinoline carboxylic acid. Each mL of VERAFLOX Oral Suspension provides 25 mg of pradofloxacin.

INDICATION

VERAFLOX is indicated for the treatment of skin infections (wounds and abscesses) in cats caused by susceptible strains of Pasteurella multocida, Streptococcus canis, Staphylococcus aureus, Staphylococcus felis, and Staphylococcus pseudintermedius.

DOSAGE AND ADMINISTRATION

Shake well before use. To ensure a correct dosage, body weight should be determined as accurately as possible. The dose of VERAFLOX is 7.5 mg/kg (3.4 mg/lb) body weight once daily for 7 consecutive days. Use the syringe provided to ensure accuracy of dosing to the nearest 0.1 mL. Rinse syringe between doses.

A sample of the lesion should be obtained for culture and susceptibility testing prior to beginning antibacterial therapy. Once results become available, continue with appropriate therapy. If acceptable response to treatment is not observed, or if no improvement is seen within 3 to 4 days, then the diagnosis should be re-evaluated and appropriate alternative therapy considered.

CONTRAINDICATIONS

DO NOT USE IN DOGS. Pradofloxacin has been shown to cause bone marrow suppression in dogs. Dogs may be particularly sensitive to this effect, potentially resulting in severe thrombocytopenia and neutropenia.

Quinolone-class drugs have been shown to cause arthropathy in immature animals of most species tested, the dog being particularly sensitive to this side effect.

Pradofloxacin is contraindicated in cats with a known hypersensitivity to quinolones.

WARNINGS

Human Warnings:

Not for human use. Keep out of reach of children.

Individuals with a history of quinolone hypersensitivity should avoid this product. Avoid contact with eyes and skin. In case of ocular contact, immediately flush eyes with copious amounts of water. In case of dermal contact, wash skin with soap and water immediately for at least 20 seconds. Consult a physician if irritation persists following ocular or dermal exposure, or in case of accidental ingestion. In humans, there is a risk of photosensitization within a few hours after exposure to quinolones. If excessive accidental exposure occurs, avoid direct sunlight. Do not eat, drink or smoke while handling this product.

It is recommended that used syringes be kept out of reach of children and disposed of properly.

Animal Warnings:

For use in cats only.

The administration of pradofloxacin for longer than 7 days induced reversible leukocyte, neutrophil, and lymphocyte decreases in healthy, 12-week-old kittens (see Animal Safety section). If an unexplained drop in leukocyte, neutrophil, and/or lymphocyte counts is noted during pradofloxacin therapy, discontinuation of treatment is recommended.

PRECAUTIONS

Prescribing antibacterial drugs in the absence of a proven or strongly suspected bacterial infection is unlikely to provide benefit to treated animals and may increase the risk of the development of drug-resistant animal pathogens.

The use of fluoroquinolones in cats has been associated with the development of retinopathy and/or blindness. Such products should be used with caution in cats.

Quinolones have been shown to produce erosions of cartilage of weight-bearing joints and other signs of arthropathy in immature animals of various species.

The safety of pradofloxacin in immune-compromised cats (i.e., cats infected with feline leukemia virus and/or feline immunodeficiency virus) has not been evaluated.

Quinolones should be used with caution in animals with known or suspected central nervous system (CNS) disorders. In such animals, quinolones have, in rare instances, been associated with CNS stimulation that may lead to convulsive seizures.

The safety of pradofloxacin in cats younger than 12 weeks of age has not been evaluated.

The safety of pradofloxacin in cats that are used for breeding or that are pregnant and/or lactating has not been evaluated.

DRUG INTERACTIONS: Compounds (e.g., sucralfate, antacids and multivitamins) containing divalent and trivalent cations (e.g., iron, aluminum, calcium, magnesium, and zinc) may substantially interfere with the absorption of quinolones resulting in a decrease in product bioavailability. Therefore, the concomitant oral administration of quinolones with foods, supplements, or other preparations containing these compounds should be avoided.

The dosage of theophylline should be reduced when used concurrently with quinolones. Cimetidine has been shown to interfere with the metabolism of quinolones and should be used with care when used concurrently. Concurrent use of quinolones with oral cyclosporine should be avoided. Concurrent administration of quinolones may increase the action of oral anticoagulants.

ADVERSE REACTIONS

In a multi-site field study, 282 cats (ages 0.3 to 19 years) were evaluated for safety when given either VERAFLOX at a dose of 7.5 mg/kg (3.4 mg/lb) or placebo (vehicle without active ingredient) at a dose of 0.14 mL/lb (0.3 mL/kg). Each group was treated once daily for 7 consecutive days. Adverse reactions are summarized in Table 1.

Table 1: Number of Adverse Reactions Among Cats Treated with Pradofloxacin (N=190) or Vehicle (N=92)*
Adverse Reactions | Pradofloxacin | Vehicle
Diarrhea / loose stools | 7 | 2
Leukocytosis with neutrophilia | 4 | 6
Elevated CPK levels | 4 | 4
Sneezing | 4 | 1
Hematuria | 2 | 2
Hypersalivation | 2 | 1
Pruritus | 2 | 0
Inappetence | 1 | 3
Lethargy | 1 | 2
Cardiac murmur | 1 | 1
Reclusive behavior | 1 | 1
Vomiting | 1 | 1
Bacteriuria | 1 | 0
Lymphadenopathy | 1 | 0
Polydipsia | 1 | 0
Upper respiratory infection | 1 | 0
* Some cats may have experienced more than one adverse reaction or more than one occurrence of the same adverse reaction during the study.

The Safety Data Sheet (SDS) provides additional occupational safety information.

CONTACT INFORMATION

For product questions, to report adverse reactions, or for a copy of the Safety Data Sheet (SDS), call Elanco Product & Veterinary Support at 888-545-5973.

For additional information about reporting adverse drug experiences for animal drugs, contact FDA at 1-888-FDA-VETS or http://www.fda.gov/reportanimalae.

CLINICAL PHARMACOLOGY

Pharmacokinetics:

Pradofloxacin is rapidly absorbed following oral administration of VERAFLOX to fasted cats, with peak serum concentrations occurring in less than 1 hour. However, food markedly diminishes the serum bio-availability of pradofloxacin; mean peak serum concentrations (Cmax) are reduced 53% and mean exposures (AUC) are decreased by 26%. The relative bioavailability of pradofloxacin, when administered as the 2.5% oral suspension to fed and fasted cats, is provided in Table 2 and Figure 1.

Table 2. Mean (1 SD) serum pradofloxacin derived pharmacokinetics parameters in cats (N =12) following a 5mg/kg oral dose of VERAFLOX under fasted and fed conditions.
 | VERAFLOX 5 mg/kg Dose
Parameter | Fasted | Fed
Cmax (ng/mL) | 2116 (549) | 999 (400)
Tmax (hr) | 0.8 | 1.4
AUC0-24 | 9111 (1939) | 6745 (1524)
Half-Life (hr) | 7.3 (1.7) | 6.4 (1.2)

Approximately 30% of the total drug concentrations are bound to plasma proteins in drug concentrations ranging from 150 to 1500 ng/mL. Dose proportional increases in drug concentrations are observed when the oral suspension is administered to fasted cats in doses ranging from 2.5 mg/kg to 10 mg/kg. Due to its short elimination half life, there is minimal pradofloxacin accumulation following multiple daily administrations.

Pharmacodynamics:

Pharmacodynamics was determined using in vitro susceptibility that showed the pathogens Pasteurella multocida, Staphylococcus pseudintermedius, and Streptococcus spp. had a pradofloxacin MIC90 of ≤0.015 to 0.12 ug/mL. The pharmacodynamics metrics (Cmax/ MIC90 and AUC/MIC90) were estimated using linear regression analysis of free drug steady-state pradofloxacin pharmacokinetics parameters from fasted cats and a pradofloxacin MIC90 value of 0.12 ug/mL. The 95% Confidence Intervals about predicted mean Cmax/MIC90 and AUC/MIC90 values were 15 to 17 and 70 to 81, respectively. It was concluded that the magnitude of the Cmax/ MIC90 and AUC/MIC90 values is predictive of product effectiveness when an oral dose of 7.5 mg/kg body weight of the pradofloxacin liquid formulation is administered to fasted cats. In addition, effectiveness was shown for cats dosed at 7.5 mg/kg body weight and fed free choice, or within two hours of dosing, in a field study.

Microbiology:

VERAFLOX is bactericidal, with activity against Gram-negative, Gram-positive, and anaerobic bacteria. The mechanism of action is dual targeting through inhibition of DNA gyrase and topoisomerase IV.

The minimum inhibitory concentrations (MICs) for pradofloxacin against Pasteurella multocida, Streptococcus canis, Staphylococcus aureus, Staphylococcus felis, and Staphylococcus pseudintermedius isolated from skin infections (wounds and abscesses) in cats in a U.S. field study from 2008 to 2009 are listed in Table 3. Only two isolates from two pradofloxacin Treatment Failure cases had elevated pradofloxacin MICs (non-hemolytic Staph. aureus - MIC = 2 μg/mL; E. coli - MIC = 4 μg/mL).

Table 3. Activity of VERAFLOX against Pathogens Isolated from Cats Treated with VERAFLOX in a Clinical Trial in the US in 2008.
Disease | Pathogen | Clinical Treatment Outcome | Number of Isolates | Sample Collection (Time Relative to Treatment) | MIC50 μg/mL | MIC90 μg/mL | MIC Range μg/mL
Skin Infections | Pasteurella multocida | Success | 40 | Pre-Treatment | 0.008 | 0.015 | ≤ 0.004 - 0.03
Skin Infections | Pasteurella multocida | Failure | 11 | Pre-Treatment | 0.008 | 0.008 | ≤ 0.004 - 0.015
Skin Infections | Streptococcus canis | Success | 13 | Pre-Treatment | 0.12 | 0.12 | 0.03 - 0.25
Skin Infections | Streptococcus canis | Failure | 2 | Pre-Treatment |  |  | 0.06 - 0.12
Skin Infections | Staphylococcus aureus | Success | 10 | Pre-Treatment | 0.12 | 0.12 | 0.015 - 0.12
Skin Infections | Staphylococcus aureus | Failure | 0
Skin Infections | Staphylococcus felis | Success | 13 | Pre-Treatment | 0.03 | 0.06 | 0.03 - 0.12
Skin Infections | Staphylococcus felis | Failure | 1 | Pre-Treatment |  |  | 0.06
Skin Infections | Staphylococcus pseud- intermedius | Success | 10 | Pre-Treatment | 0.06 | 0.06 | 0.03 - 0.06
Skin Infections | Staphylococcus pseud- intermedius | Failure | 1 | Pre-Treatment |  |  | 0.03

EFFECTIVENESS

The clinical effectiveness of VERAFLOX was demonstrated in a multi-site (16 sites) field study. In this masked and randomized study, the effectiveness of VERAFLOX was compared to a placebo control (vehicle without active ingredient). Of the 282 cats enrolled in this study, 190 were treated with VERAFLOX once daily at 7.5 mg/kg (3.4 mg/lb) body weight for 7 consecutive days and 92 were treated with placebo once daily at 0.3 mL/kg body weight for 7 consecutive days. The effectiveness database included 182 cats: 66 placebo (vehicle)-treated cats and 116 VERAFLOX-treated cats. The analysis of this effectiveness database showed that the cure rate was greater in the VERAFLOX group on Day 15, as summarized in Table 4. Study cure rates were determined approximately 15 days after initiation of therapy. The statistical evaluation of the primary effectiveness endpoint (Study Cures) showed that VERAFLOX was different from placebo with 73.4% VERAFLOX study cures versus 38.9% placebo study cures.

Table 4: Day 15 Case Classification
Treatment Group | Percent Cures
VERAFLOX N= 116 | 73.4%
Placebo N= 66 | 38.9%
P-value | 0.0053

ANIMAL SAFETY

Target Animal Safety Study: Safety was evaluated in 32 healthy, 12-week-old kittens administered VERAFLOX once daily at doses of 0, 7.9, 23.7, or 39.5 mg/kg (0, 1, 3, and 5 times the recommended dose) for 21 consecutive days. Additional control (0X) and high-dose (5X) animals were maintained for 45 days after treatment cessation.

There were statistically significant decreases in neutrophils, lymphocytes, and monocytes in the 3X and 5X groups compared to the controls. During the treatment period, one 3X cat and three 5X cats had absolute neutrophil counts below the reference range. Bone marrow cytology results consistent with bone marrow suppression (myeloid hypoplasia) were seen in the 3X neutropenic cat and two of the three 5X neutropenic cats. The 3X cat was neutropenic on the last day of the study prior to scheduled euthanasia, while absolute neutrophil values for the three 5X cats returned to normal either during treatment or after the cessation of treatment.

The most frequent abnormal clinical finding was soft feces. While this was seen in both treated and control groups, it was observed more frequently in the 3X and 5X kittens.

Ocular Safety Study: Ocular safety was evaluated in 20 healthy adult cats using pradofloxacin in capsules administered orally, once daily at doses of 30 mg/kg and 50 mg/kg for 23 days. No effects were seen in the following investigated ocular parameters: ophthalmic examinations, ERGs, and optical coherence tomography. Cats receiving 50 mg/kg/day of pradofloxacin showed mild weight loss. Cats receiving 30 and 50 mg/kg/day of pradofloxacin exhibited hypersalivation and vomiting throughout the study. Dose-dependent reductions in white blood cell counts were noted in the pradofloxacin-treated cats. One cat receiving 30 mg/kg/day of pradofloxacin exhibited minimal photoceptor degeneration on light and electron microscopy of a type that differed from enrofloxacin-treated cats (comparator used in this study); the effects of pradofloxacin on these retinal changes is unknown.

Pilot Toxicity Study: In an oral toxicity study, 4 cats received pradofloxacin at 50 mg/kg/day for 25 days. All cats exhibited vomiting and hypersalivation. One cat exhibited fluoroquinolone-induced neurologic signs (decreased mobility, staggering, and vocalization) on Day 5 of the study.

STORAGE CONDITIONS

Store below 30°C (86°F).

After initial opening, VERAFLOX has demonstrated in-use stability of 60 days.

HOW SUPPLIED

Bottle Size

15 mL

Approved by FDA under NADA # 141-344

© 2025 Elanco or its affiliates.

Veraflox, Elanco and the diagonal bar logo are trademarks of Elanco or its affiliates

Manufactured for:
Elanco US Inc.
Indianapolis, IN 46221 U.S.A.

Revised: August 2025

Elanco™

PA513324X

PRINCIPAL DISPLAY PANEL – 15 mL

Elanco™

Veraflox™

(pradofloxacin)

Oral Suspension for Cats

25 mg/mL

Manufactured for:
Elanco US Inc.
Indianapolis, IN 46221 U.S.A.
Approved by FDA under NADA # 141-344

15 mL

Elanco

Veraflox™

(pradofloxacin)

Oral Suspension for Cats

25 mg/mL

15 mL